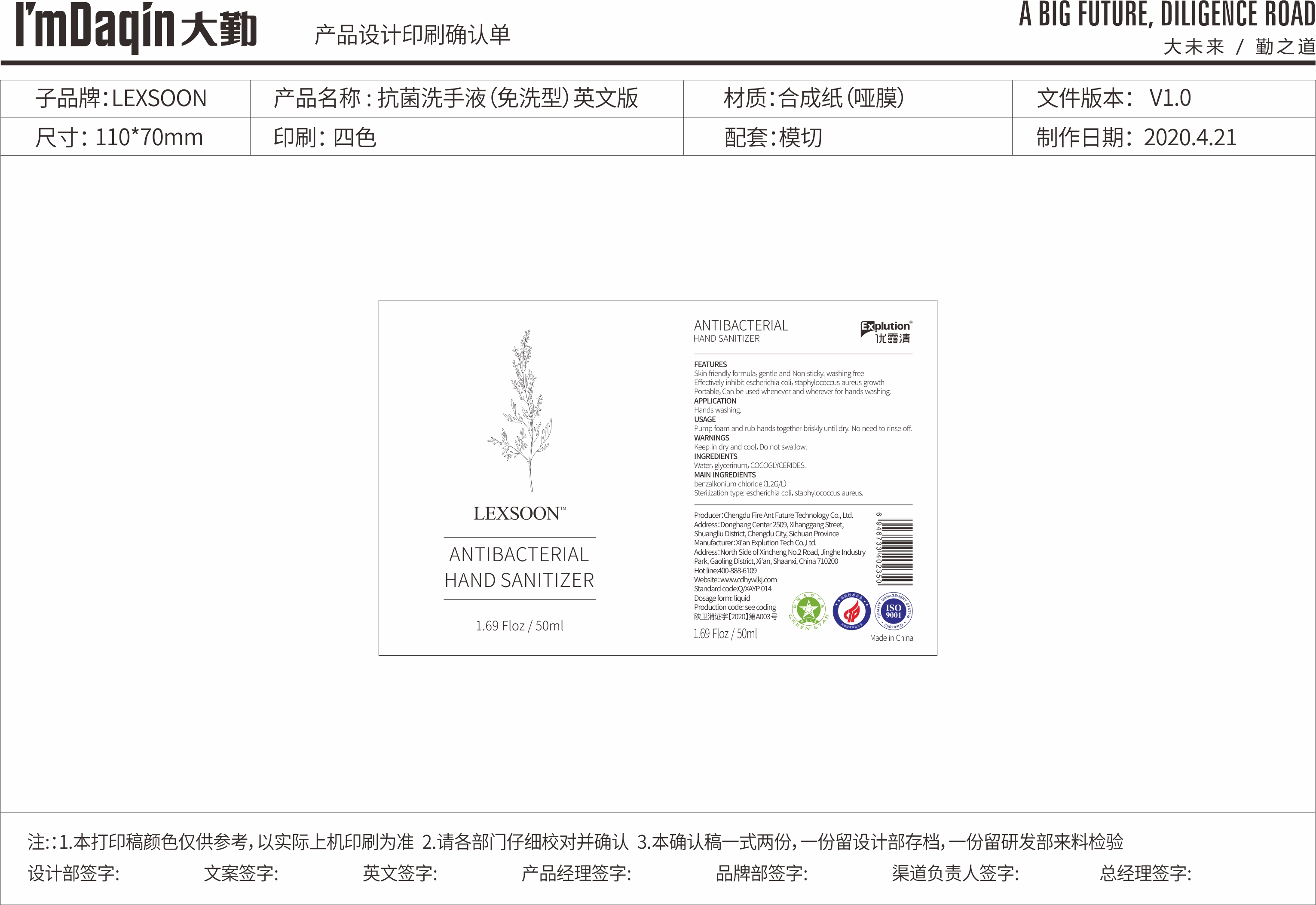 DRUG LABEL: ANTIBACTERIAL HAND SANITIZER
NDC: 75709-004 | Form: LIQUID
Manufacturer: Xi'an Explution Tech Co.,Ltd.
Category: otc | Type: HUMAN OTC DRUG LABEL
Date: 20200430

ACTIVE INGREDIENTS: BENZALKONIUM CHLORIDE 1.2 g/1 mL
INACTIVE INGREDIENTS: COCO-GLYCERIDES; GLYCERIN; WATER

ANTIBACTERIAL HAND SANITIZER

Active Ingredient

benzalkonium chloride(1.2G/L)

USAGE

Pump foam and rub hands together briskly until dry.No need to rinse off.

WARNINGS

Keep in dry and cool, Do not swallow.

Inactive ingredients

Water,glycerinum, COCOGLYCERIDES.